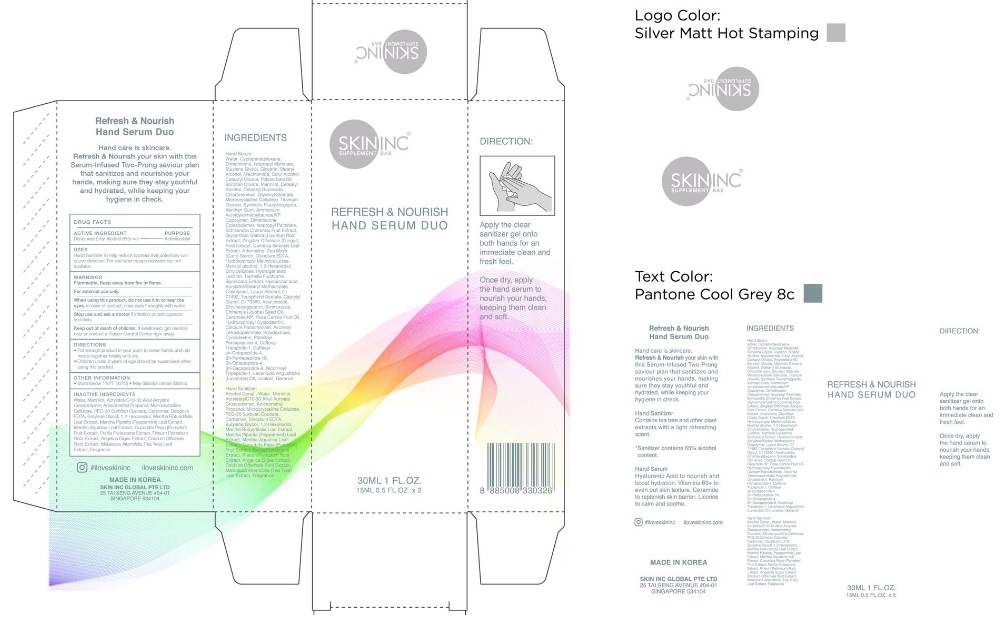 DRUG LABEL: Skininc
NDC: 80761-001 | Form: GEL
Manufacturer: Skininc Global Pte. Ltd.
Category: otc | Type: HUMAN OTC DRUG LABEL
Date: 20201007

ACTIVE INGREDIENTS: ALCOHOL 65 mL/100 mL
INACTIVE INGREDIENTS: WATER; MANNITOL; CARBOMER INTERPOLYMER TYPE A (ALLYL SUCROSE CROSSLINKED); AMINOMETHYLPROPANOL; MICROCRYSTALLINE CELLULOSE; CARBOMER HOMOPOLYMER, UNSPECIFIED TYPE; MAGNESIUM DISODIUM EDTA; EDETATE DISODIUM ANHYDROUS; BUTYLENE GLYCOL; 1,2-HEXANEDIOL; MENTHA X ROTUNDIFOLIA LEAF; MENTHA X PIPERITA WHOLE; MENTHA AQUATICA LEAF; PUMPKIN; RHEUM PALMATUM ROOT; ANGELICA GIGAS ROOT; CNIDIUM OFFICINALE ROOT; MELALEUCA ALTERNIFOLIA LEAF

SKININC

Active Ingredients

Denatured Ethyl Alcohol 65% v/v

Purpose

Antimicrobial.

Warnings

- Flammable. Keep away from fire or flame.
- For external use only.
- When using this product do not use it in or near eyes. In case of contact, rinse eyes thoroughly with water.
- Stop use and ask a doctor if irritation or rash appears and lasts.
- Keep out of reach of children. If swallowed, get medical help or contact Poison Control Center right away.

Uses

- Hand Sanitizer to help reduce bacteria that potentially can cause disease.
- For use when soap and water are not available.

Directions

- Place enough product in your palm to cover hands and rub hands together briskly until dry.
- Children under 6 years of age should be supervised when using this product.

Other Information

- Store below 110^0F(43^0C)
- May discolour certain fabrics.

Inactive Ingredient

Water,Mannitol,Acrylates/C10-30 Alkyl Acrylate Crosspolymer,Aminomethyl Propanol,Microcrystalline Cellulose,PEG-20 Sorbitan Cocoate,Carbomer,Disodium EDTA,Butylene Glycol,1,2-Hexanediol,Mentha Rotundifolia Leaf Extract,Mentha Piperita (Peppermint) Leaf Extract,Mentha Aquatica Leaf Extract,Cucurbita Pepo (Pumpkin) Fruit Extract,Perilla Frutescens Extract,Rheum Palmatum Root Extract,Angelica Gigas Extract,Cnidium Officinale Root Extract,Melaleuca Alternifolia (Tea Tree) Leaf Extract, Fragrance